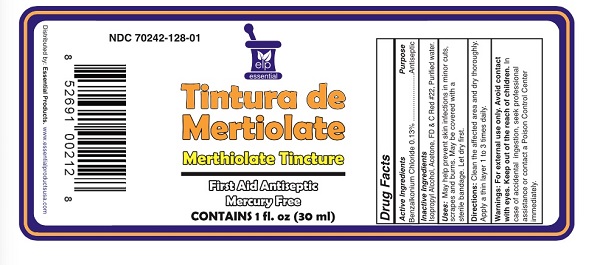 DRUG LABEL: Tintuta de Mentiolate/Menthiolate Tincture
NDC: 70242-128 | Form: SOLUTION
Manufacturer: Dannso Corp./d.b.a. Essential Products
Category: otc | Type: HUMAN OTC DRUG LABEL
Date: 20230101

ACTIVE INGREDIENTS: BENZALKONIUM CHLORIDE 0.13 g/1 mL
INACTIVE INGREDIENTS: ACETONE; ALCOHOL; D&C RED NO. 22; WATER

Tincture Merthiolate

Active Ingredients Purpose

Benzalkonium Chloride (0.13%) ................... Antiseptic

Use

May help prevent skin infection in

- minor cuts
- scrapes
- burns

Keep out of reach of children. If swallowed, get medical help or contact a Poison Control Center right away.

INDICATIONS AND USAGE

Antiseptic

For External Use Only

Directions

- clean the affected area
- and dry thoroughly. Apply a thin layer 1 to 3 times daily.
- May be covered with a sterile bandage, let dry first.

Warnings For external use only

Avoid Contact with eyes.

When using this product

INACTIVE INGREDIENT

Inactive Ingredients Acetone, FD&C red # 22, Isopropyl Alcohol, Purified Water.